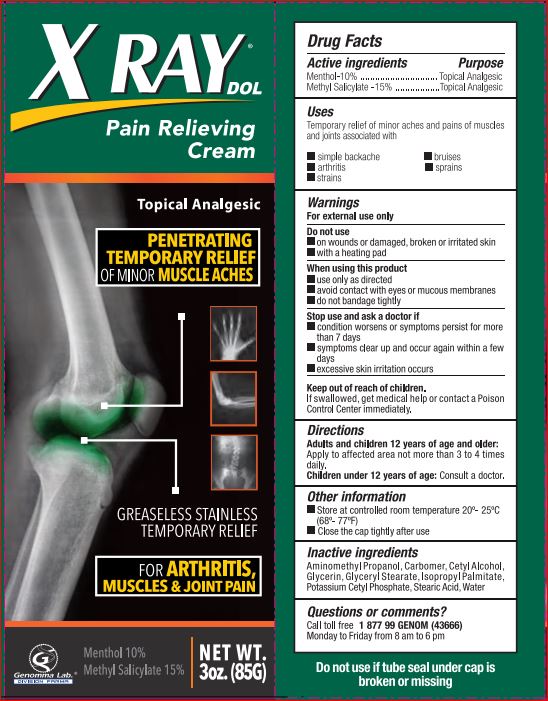 DRUG LABEL: X Ray Pain Relieving
NDC: 50066-501 | Form: CREAM
Manufacturer: Genomma Lab
Category: otc | Type: HUMAN OTC DRUG LABEL
Date: 20180405

ACTIVE INGREDIENTS: Menthol 10 g/100 mL; Methyl Salicylate 15 g/100 mL
INACTIVE INGREDIENTS: AMINOMETHYLPROPANOL; CARBOMER HOMOPOLYMER TYPE C (ALLYL PENTAERYTHRITOL CROSSLINKED); Cetyl Alcohol; Glycerin; GLYCERYL MONOSTEARATE; Isopropyl Palmitate; Potassium Cetyl Phosphate; Stearic Acid; water

Drug Facts

Active ingredients Purpose

Menthol-10% .................................... Topical Analgesic
Methyl Salicylate -15% .....................Topical Analgesic

Uses

Temporary relief of minor aches and pains of muscles

and joints associated with

- simple backache
- bruises
- arthritis
- sprains
- strains

Warnings

For external use only

Do not use

- on wounds or damaged, broken or irritated skin
- with heating pad

When using this product

- use only as directed

- avoid contact with eyes or mucous membranes

- do not bandage tightly

Stop use and ask a doctor if

- condition worsens or symptoms persist for more than 7 days

- symptoms clear up and occur again within a few days

- excessive skin irritation occurs

Keep out of reach of children. If swallowed, get medical help or contact a Poison Control Center immediately

Directions

Adults and children 12 years of age and older: Apply to affected area not more than 3 to 4 times daily.
Children under 12 years of age: Consult a doctor.

INACTIVE INGREDIENT

Aminomethyl Propanol,Carbomer,Cetyl Alcohol,Glycerin,Glyceryl Stearate,Isopropyl Palmitate,Potassium Cetyl Phosphate,Stearic Acid,Water